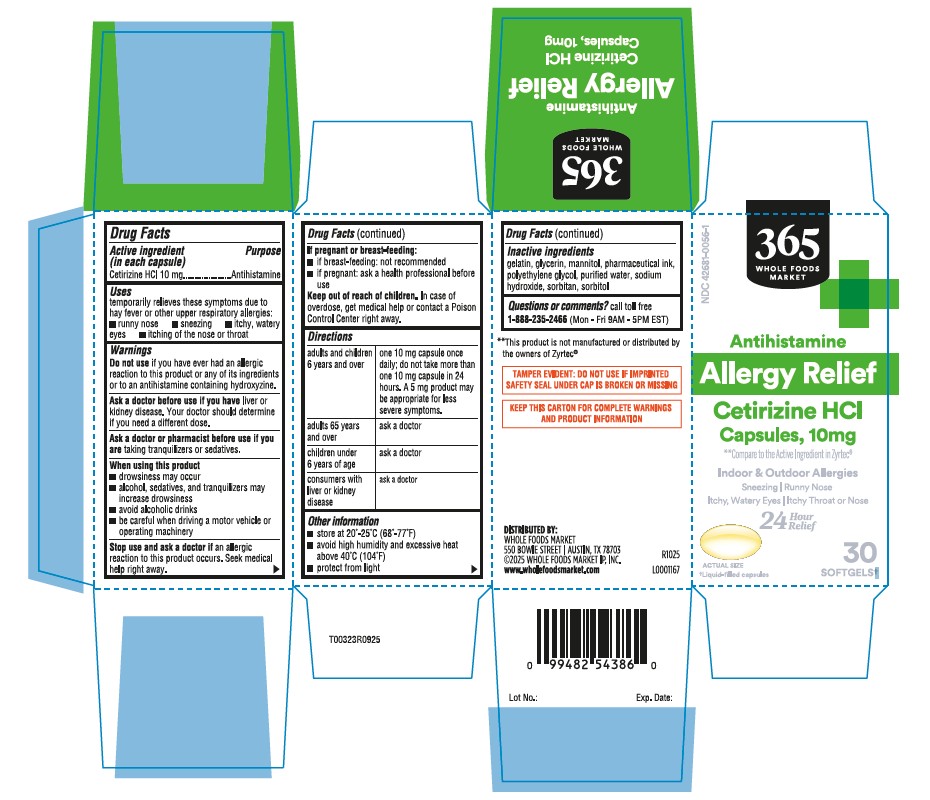 DRUG LABEL: Allergy Relief
NDC: 42681-0056 | Form: CAPSULE
Manufacturer: Whole Foods Market, INC.
Category: otc | Type: HUMAN OTC DRUG LABEL
Date: 20251208

ACTIVE INGREDIENTS: CETIRIZINE HYDROCHLORIDE 10 mg/1 1
INACTIVE INGREDIENTS: GELATIN; GLYCERIN; MANNITOL; POLYETHYLENE GLYCOL, UNSPECIFIED; WATER; SODIUM HYDROXIDE; SORBITAN; SORBITOL

Cetirizine HCl Capsules, 10 mg dye free-whole foods

Active ingredient (in each capsule)

Cetirizine HCl 10 mg

Purpose

Antihistamine

Uses

temporarily relieves these symptoms due to hay fever or other upper respiratory allergies:

■ runny nose ■ sneezing ■ itchy, watery eyes ■ itching of the nose or throat

Warnings

Do not use

if you have ever had an allergic reaction to this product or any of its ingredients or to an antihistamine containing hydroxyzine.

Ask a doctor before use if you have

liver or kidney disease. Your doctor should determine if you need a different dose.

Ask a doctor or pharmacist before use if you are

taking tranquilizers or sedatives.

When using this product

- drowsiness may occur
- alcohol, sedatives, and tranquilizers may increase drowsiness
- avoid alcoholic drinks
- be careful when driving a motor vehicle or operating machinery

Stop use and ask a doctor if

an allergic reaction to this product occurs. Seek medical help right away.

If pregnant or breast-feeding:

- if breast-feeding: not recommended
- if pregnant: ask a health professional before use

Keep out of reach of children.

In case of overdose, get medical help or contact a Poison Control Center right away.

Directions

adults and children 6 years and over | one 10 mg capsule once daily; do not take more than one 10 mg capsule in 24 hours. A 5 mg product may be appropriate for less severe symptoms.
adults 65 years and over | ask a doctor
children under 6 years of age | ask a doctor
consumers with liver or kidney disease | ask a doctor

Other information

- store at 20º-25ºC (68º-77ºF)
- avoid high humidity and excessive heat above 40ºC (104ºF)
- protect from light

Inactive ingredients

gelatin, glycerin, mannitol, pharmaceutical ink, polyethylene glycol, purified water, sodium hydroxide, sorbitan, sorbitol

Questions or comments?

call toll free 1-888-235-2466(Mon - Fri 9AM - 5PM EST)

*"This product is not manufactured or distributed by the owners of Zyrtec®

TAMPER EVIDENT: DO NOT USE IF IMPRINTED SAFETY SEAL UNDER CAP IS BROKEN OR MISSING

KEEP THIS CARD FOR COMPLETE WARNINGS AND PRODUCT INFORMATION

DISTRIBUTED BY:
WHOLE FOODS MARKET
550 BOWIE STREET I AUSTIN, 1X 78703
©2025 WHOLE FOODS MARKET IP, INC.
www.wholeloodsmarket.com

R1025
L0001167

Principal Display Panel-30s count

NDC 42681-0056-1

365

WHOLE FOODS

MARKET

Antihistamine

Allergy Relief

Cetitizine HCl

Capsules, 10 mg

** Compare to the Active Ingrident in Zyrtec

Indoor & Outdoor Allergies
Sneezing I Runny Nose
Itchy, Watery Eyes I Itchy Throat or Nose
24 Hour
Relief

30 SOFTGELSt

tLiquid-filled capsules